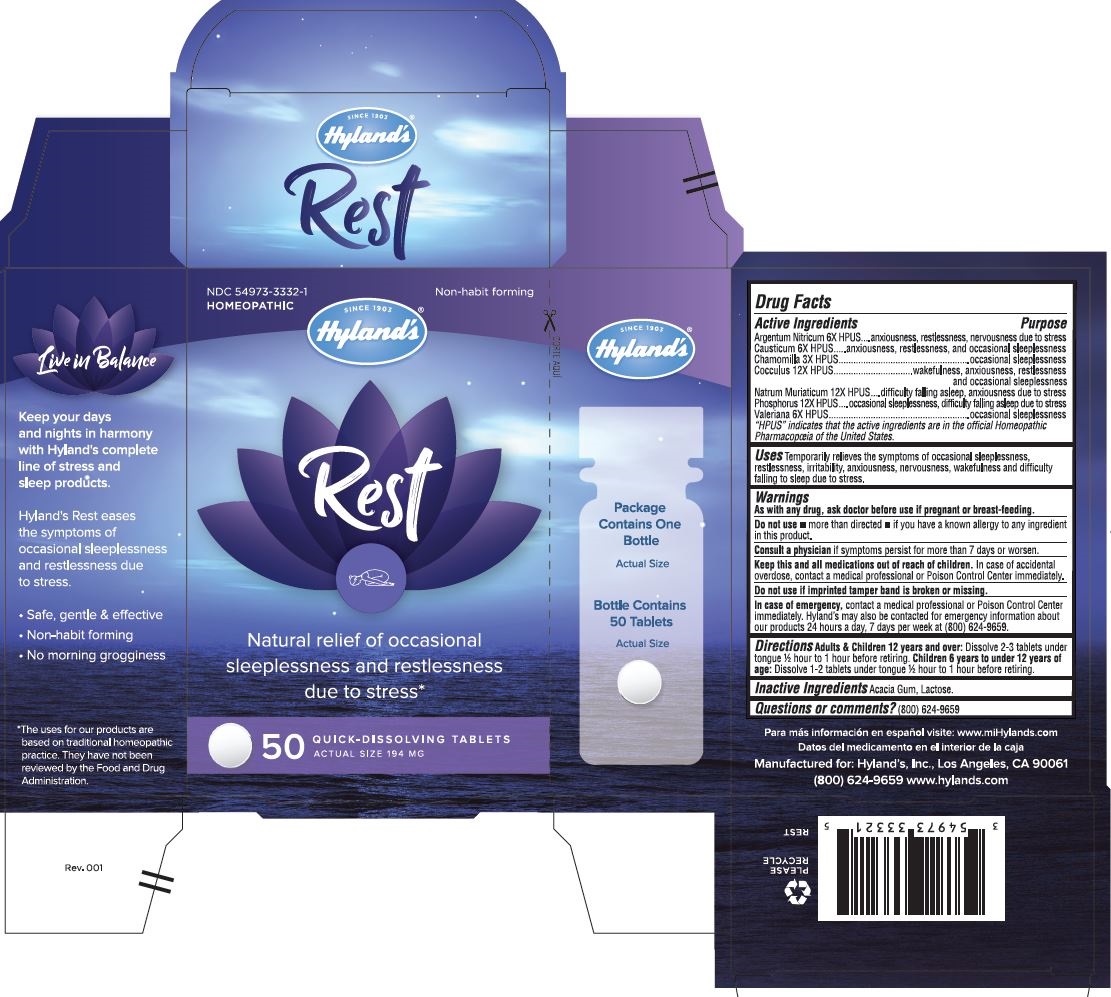 DRUG LABEL: Rest
NDC: 54973-3332 | Form: TABLET
Manufacturer: Hyland's Inc.
Category: homeopathic | Type: HUMAN OTC DRUG LABEL
Date: 20221213

ACTIVE INGREDIENTS: ANAMIRTA COCCULUS SEED 12 [hp_X]/1 1; CAUSTICUM 6 [hp_X]/1 1; VALERIAN 6 [hp_X]/1 1; SILVER NITRATE 6 [hp_X]/1 1; MATRICARIA CHAMOMILLA 3 [hp_X]/1 1; SODIUM CHLORIDE 12 [hp_X]/1 1; PHOSPHORUS 12 [hp_X]/1 1
INACTIVE INGREDIENTS: ACACIA; LACTOSE MONOHYDRATE

Rest

PURPOSE

Natural relief of occasional sleeplessness and restlessness due to stress.

Drug Facts

Active Ingredients | Purpose
Argentum Nitricum 6X HPUS | anxiousness, restlessness, nervousness due to stress
Causticum 6X HPUS | anxiousness, restlessness, and occasional sleeplessness
Chamomilla 3X HPUS | occasional sleeplessness
Cocculus 12X HPUS | wakefulness, anxiousness, restlessness and occasional sleeplessness
Natrum Muriaticum 12X HPUS | difficulty falling asleep, anxiousness due to stress
Phosphorus 12X HPUS | occasional sleeplessness, difficulty falling asleep due to stress
Valeriana 6X HPUS | occasional sleeplessness

“HPUS” indicates that the active ingredients are in the official Homeopathic Pharmacopœia of the United States.

Uses

Temporarily relieves the symptoms of occasional sleeplessness, restlessness, irritability, anxiousness, nervousness, wakefulness and difficulty falling to sleep due to stress.

WARNINGS

PREGNANCY OR BREAST FEEDING

As with any drug, ask doctor before use if pregnant or breast-feeding.

Do not use  • more than directed  • if you have a known allergy to any ingredient in this product.

ASK DOCTOR

Consult a physician if symptoms persist for more than 7 days or worsen.

KEEP OUT OF REACH OF CHILDREN

Keep this and all medications out of reach of children. In case of accidental overdose, contact a medical professional or Poison Control Center immediately.

Do not use if imprinted tamper band is broken or missing.

In case of emergency

Contact a medical professional or Poison Control Center immediately. Hyland’s may also be contacted for emergency information about our products 24 hours a day, 7 days per week at (800) 624-9659.

Directions

Adults & Children 12 years and over: Dissolve 2-3 tablets under tongue ½ hour to 1 hour before retiring.

Children 6 years to under 12 years of age: Dissolve 1-2 tablets under tongue ½ hour to 1 hour before retiring.

INACTIVE INGREDIENT

Acacia Gum, Lactose.

Questions or comments?

(800) 624-9659

PRINCIPAL DISPLAY PANEL - 50 TABLET BOTTLE CARTON

NDC 54973-3332-1

HOMEOPATHIC

Non-habit forming

SINCE 1903

Hyland's®

Rest

Natural relief of occasional

sleeplessness and restlessness

due to stress*

50 QUICK- DISSOLVING TABLETS

ACTUAL SIZE 194 MG